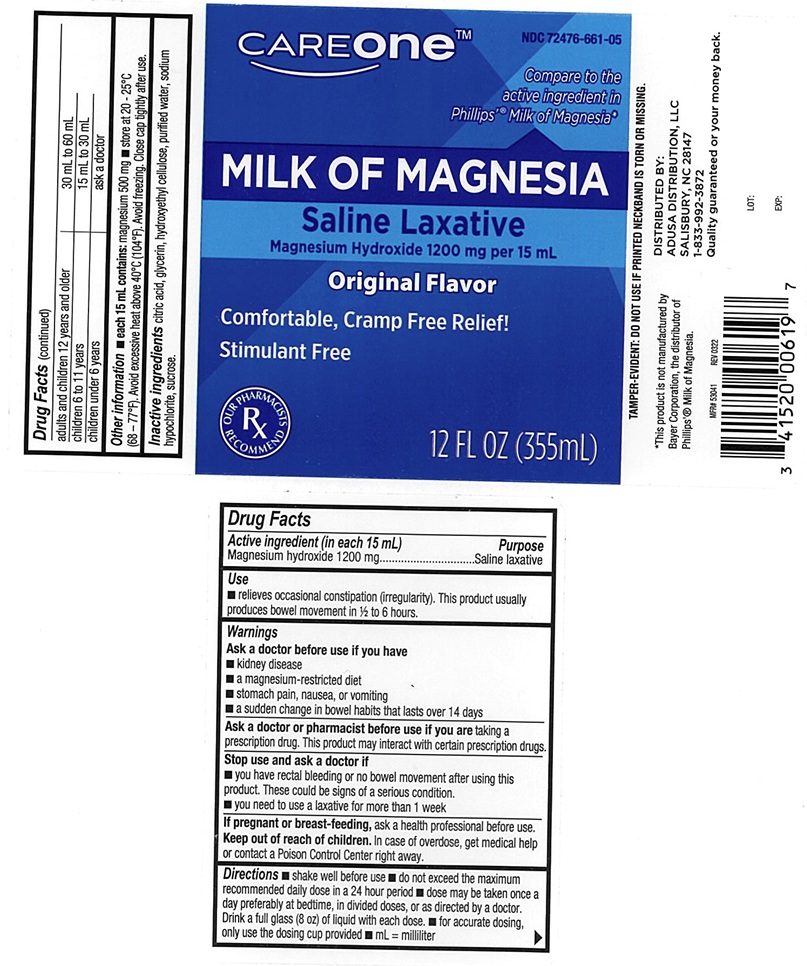 DRUG LABEL: Careone Milk of magnesia Original
NDC: 72476-661 | Form: LIQUID
Manufacturer: Retail Business Services, LLC.
Category: otc | Type: Human OTC Drug Label
Date: 20241211

ACTIVE INGREDIENTS: Magnesium Hydroxide 1200 mg/15 mL
INACTIVE INGREDIENTS: ANHYDROUS CITRIC ACID; Glycerin; HYDROXYETHYL CELLULOSE (2000 MPA.S AT 1%); water; Sodium Hypochlorite; Sucrose

CAREone Milk of Magnesia original

ACTIVE INGREDIENT(S)

Magnesium hydroxide 1200 mg

PURPOSE

Saline laxative

USE(S)

relieves occasional constipation (irregularity). This product usually produces bowel movement in 1/2 to 6 hours.

WARNINGS

.

ASK A DOCTOR BEFORE USE IF YOU HAVE

- kidney disease
- a magnesium-restricted diet
- stomach pain, nausea, or vomiting
- a sudden change in bowel habits that lasts over 14 days

ASK A DOCTOR OR PHARMACIST BEFORE USE IF YOU ARE

taking a prescription drug. This product may interact with certain prescription drugs.

STOP USE AND ASK DOCTOR IF

- you have rectal bleeding or no bowel movement after using this product. These could be signs of a serious condition.
- you need to use a laxative for more than 1 week

IF PREGNANCY OR BREAST-FEEDING,

ask a health professional before use.

KEEP OUT OF REACH OF CHILDREN

In case of overdose, get medical help or contact a Poison Control Center right away.

DIRECTIONS

- shake well before use
- do not exceed the maximum recommended daily dose in a 24 hour period
- dose may be taken once a day preferably at bedtime, in divided doses, or as directed by a doctor. Drink a full glass (8 OZ) of liquid with each dose.
- for accurate dosing, only use the dosing cup provided
- mL=milliliter

adults and children 12 years and older | 30 mL to 60 mL
children 6 to 11 years | 15 mL to 30 mL
children under 6years | ask a doctor

OTHER INFORMATION

- each 15 mL contains: magnesium 500 mg
- store at 20 - 25oC (68 - 77oF), Avoid excessive heat above 40oC(104oF). Avoid freezing. Close cap tightly after use.

INACTIVE INGREDIENTS

citric acid, glycerin, hydroxyethyl cellulose, purified water, sodium hypochlorite, sucrose.

PRINCIPAL DISPLAY PANEL

CAREone TM

NDC : 72476-661-05

Compare to the active ingredients in Phillips'® Milk of Magnesia*

MILK OF MAGNESIA

Saline Laxative

Magnesium Hydroxide 1200 mg per 15 mL

Original Flavor

Comfortable, Cramp Free Relief!

Stimulant Free

12FL OZ (355 mL)